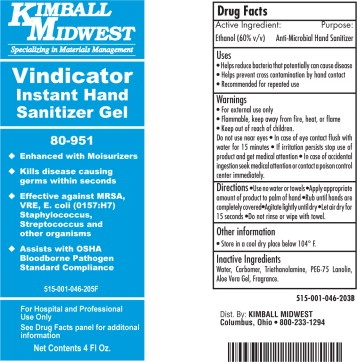 DRUG LABEL: Vindicator Instant Hand Sanitizer
NDC: 66608-515 | Form: GEL
Manufacturer: Kimball Midwest 
Category: otc | Type: HUMAN OTC DRUG LABEL
Date: 20251216

ACTIVE INGREDIENTS: alcohol 600 mL/1000 mL
INACTIVE INGREDIENTS: water; CARBOMER HOMOPOLYMER TYPE C (ALLYL PENTAERYTHRITOL CROSSLINKED); aloe; trolamine

Vindicator
Instant Hand Sanitizer Gel

Active Ingredient:

Ethanol (60% v/v)

Purpose:

Anti-Microbial Hand Sanitizer

Uses

- Helps reduce bacteria that potentially can cause disease
- Helps prevent cross contamination by hand contact
- Recommended for repeated use

Warnings

- For external use only
- Flammable, keep away from fire, heat, or flame

Keep out of reach of children.
Do not use near eyes • In case of eye contact flush with water for 15 minutes • If irritation persists stop use of product and get medical attention • In case of accidental ingestion seek medical attention or contact a poison control center immediately.

Directions

- Use no water or towels
- Apply appropriate amount of product to palm of hand
- Rub until hands are completely covered
- Agitate lightly until dry
- Let air dry for 15 seconds
- Do not rinse or wipe with towel.

Other Information

- Store in a cool dry place below 104° F.

Inactive Ingredients

Water, Carbomer, Triethanolamine, PEG-75 Lanolin, Aloe Vera Gel, Fragrance.

Kimball Midwest

Specializing in Materials Management

Vindicator

Instant Hand Sanitizer Gel
• Enhanced with Moisturizers• Kills disease causing germs within seconds• Effective against MRSA, VRE, E. coli (0157:H7) Staphylococcus, Streptococcus and other organisms• Assists with OSHA Bloodborne Pathogen Standard Compliance

For Hospital and Professional Use Only

See Drug Facts panel for additional information